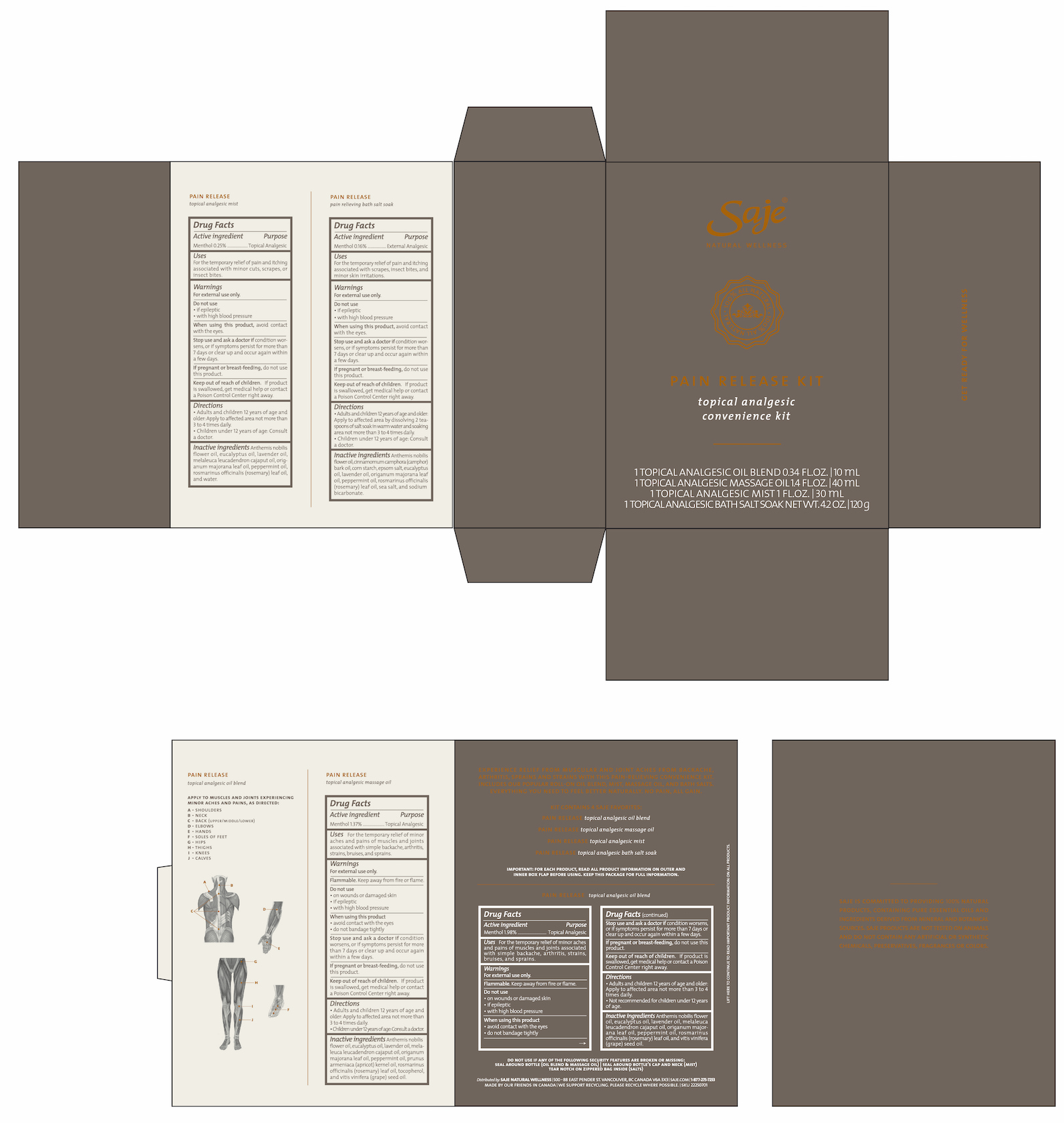 DRUG LABEL: Pain Release
NDC: 70983-010 | Form: KIT | Route: TOPICAL
Manufacturer: Saje Natural Business Inc.
Category: otc | Type: HUMAN OTC DRUG LABEL
Date: 20260113

ACTIVE INGREDIENTS: MENTHOL 17.62 mg/1 mL; MENTHOL 12.19 mg/1 mL; MENTHOL 2.23 mg/1 mL; MENTHOL 1.6 mg/1 g
INACTIVE INGREDIENTS: CHAMAEMELUM NOBILE FLOWER OIL; EUCALYPTUS OIL; LAVENDER OIL; CAJUPUT OIL; SWEET MARJORAM OIL; PEPPERMINT OIL; ROSEMARY OIL; GRAPE SEED OIL; CHAMAEMELUM NOBILE FLOWER OIL; EUCALYPTUS OIL; LAVENDER OIL; CAJUPUT OIL; SWEET MARJORAM OIL; PEPPERMINT OIL; APRICOT KERNEL OIL; ROSEMARY OIL; TOCOPHEROL; GRAPE SEED OIL; CHAMAEMELUM NOBILE FLOWER OIL; EUCALYPTUS OIL; LAVENDER OIL; CAJUPUT OIL; SWEET MARJORAM OIL; PEPPERMINT OIL; ROSEMARY OIL; WATER; CHAMAEMELUM NOBILE FLOWER OIL; CAMPHOR OIL; STARCH, CORN; MAGNESIUM SULFATE HEPTAHYDRATE; EUCALYPTUS OIL; LAVENDER OIL; SWEET MARJORAM OIL; PEPPERMINT OIL; ROSEMARY OIL; SEA SALT; SODIUM BICARBONATE

Pain Release Kit - Topical Analgesic Convenience Kit

GET READY FOR WELLNESS

Experience relief from muscular and joint aches from backache, arthritis, sprains and strains with this pain-relieving convenience kit. Includes our popular roll-on oil blend, mist, massage oil, and bath salts. Everything you need to feel better naturally. No pain, all gain.

Kit Contains 4 Saje Favorites:

PAIN RELEASE topical analgesic oil blend

PAIN RELEASE topical analgesic massage oil

PAIN RELEASE topical analgesic mist

PAIN RELEASE topical analgesic bath salt soak

IMPORTANT: FOR EACH PRODUCT, READ ALL PRODUCT INFORMATION ON OUTER AND INNER BOX FLAP BEFORE USING. KEEP THIS PACKAGE FOR FULL INFORMATION.

DO NOT USE IF ANY OF THE FOLLOWING SECURITY FEATURES ARE BROKEN OR MISSING:
SEAL AROUND BOTTLE (OIL BLEND & MASSAGE OIL) | SEAL AROUND BOTTLE'S CAP AND NECK (MIST) | TEAR NOTCH ON ZIPPERED BAG INSIDE (SALTS)

Distributed by: SAJE NATURAL WELLNESS | 500 - 88 East Pender St. Vancouver, BC Canada V6A 3X3 | saje.com | 1-877-275-7253 | Made by our friends in Canada

We support recycling. Please recycle where possible

SKU 22250701

Lift here to continue to read important product information on all products.

PAIN RELEASE topical analgesic oil blend Drug Facts Active ingredient

Menthol 1.98%

Purpose Topical Analgesic

Uses For the temporary relief of minor aches and pains of muscles and joints associated with simple backache, arthritis, strains, bruises, and sprains.

Warnings

For external use only.

Flammable. Keep away from fire or flame.

Do not use

- on wounds or damaged skin
- if epileptic
- with high blood pressure

When using this product

- avoid contact with the eyes
- do not bandage tightly

Stop use and ask a doctor if

condition worsens, or if symptoms persist for more than 7 days or clear up and occur again within a few days.

If pregnant or breastfeeding,

do not use this product.

Keep out of reach of children.

If product is swallowed, get medical help or contact a Poison Control Center right away.

Directions

- Adults and children 12 years of age and older: Apply to affected area

DOSAGE AND ADMINISTRATION

not more than 3 to 4 times daily.

- Not recommended for children under 12 years of age.

Inactive ingredients

Anthemis nobilis flower oil, eucalyptus oil, lavender oil, melaleuca leucadendron cajaput oil, origanum majorana leaf oil, peppermint oil, rosmarinus officinalis (rosemary) leaf oil, and vitis vinifera (grape) seed oil.

PAIN RELEASE topical analgesic oil blend

Apply to muscles and joints experiencing minor aches and pains, as directed:

A - Shoulders

B - Neck

C - Back

D - Elbows

E - Hands

F - Soles of feet

G - Hips

H - Thighs

I - Knees

J - Calves

PAIN RELEASE topical analgesic massage oil Drug Facts Active ingredient

Menthol 1.37%

Purpose Topical Analgesic

Uses For the temporary relief of minor aches and pains of muscles and joints associated with simple backache, arthritis, strains, bruises, and sprains

Warnings

For external use only.

Flammable. Keep away from fire or flame.

Do not use

- on wounds or damaged skin
- if epileptic
- with high blood pressure

When using this product,

- avoid contact with the eyes
- do not bandage tightly

Stop use and ask a doctor if

condition worsens, or if symptoms persist for more than 7 days or clear up and occur again within a few days.

If pregnant or breast-feeding,

do not use this product

Keep out of reach of children.

If product is swallowed, get medical help or contact a Poison Control Center right awa y.

Directions

- Adults and children 12 years of age and older: Apply to affected area

DOSAGE AND ADMINISTRATION

not more than 3 to 4 times daily

- Children under 12 years of age: Consult a doctor.

Inactive ingredients

Anthemis nobilis flower oil, eucalyptus oil, lavender oil, melaleuca leucadendron cajaput oil, origanum majorana leaf oil, peppermint oil, prunus armeniaca (apricot) kernel oil, rosmarinus officinalis (rosemary) leaf oil, tocopherol, and vitis vinifera (grape) seed oil.

PAIN RELEASE topical analgesic mist Drug Facts Active ingredient

Menthol 0.25%

Purpose Topical Analgesic

Uses For the temporary relief of pain and itching associated with minor cuts, scrapes, or insect bites

Warnings

For external use only.

Do not use

- if epileptic
- with high blood pressure

When using this product,

avoid contact with the eyes.

Stop use and ask a doctor if

condition worsens, or if symptoms persist for more than 7 days or clear up and occur again within a few days.

If pregnant or breastfeeding,

do not use this product

Keep out of reach of children.

If product is swallowed, get medical help or contact a Poison Control Center right away.

Directions

- Adults and children 12 years of age and older: Apply to affected area

DOSAGE AND ADMINISTRATION

not more than 3 to 4 times daily

- Children under 12 years of age: Consult a doctor.

Inactive ingredients

Anthemis nobilis flower oil, eucalyptus oil, lavender oil, melaleuca leucadendron cajaput oil, origanum majorana leaf oil, peppermint oil, rosmarinus officinalis (rosemary) leaf oil, and water.

PAIN RELEASE pain relieving bath salt soak Drug Facts Active ingredient

Menthol 0.16%

Purpose External Analgesic

Uses For the temporary relief of pain and itching associated with scrapes, insect bites, and minor skin irritations.

Warnings

For external use only.

Do not use

- if epileptic
- with high blood pressure

When using this product,

avoid contact with the eyes.

Stop use and ask a doctor if

condition worsens, or if symptoms persist for more than 7 days or clear up and occur again within a few days.

If pregnant or breast-feeding,

do not use this product.

Keep out of reach of children.

If product is swallowed, get medical help or contact a Poison Control Center right away.

Directions

- Adults and children 12 years of age and older: Apply to affected area

DOSAGE AND ADMINISTRATION

by dissolving 2 teaspoons of salt soak in warm water and soaking area not more than 3 to 4 times daily.

- Children under 12 years of age: Consult a doctor.

Inactive ingredients

Anthemis nobilis flower oil, cinnamomum camphora (camphor) bark oil, corn starch, epsom salt, eucalyptus oil, lavender oil, origanum majorana leaf oil, peppermint oil, rosmarinus officinalis (rosemary) leaf oil, sea salt, and sodium bicarbonate.

PACKAGE LABEL

Saje Natural Wellness

PAIN RELEASE KIT

topical analgesic convenience kit

1 TOPICAL ANALGESIC OIL BLEND 0.34 FL.OZ. | 10 mL

1 TOPICAL ANALGESIC MASSAGE OIL 1.4 FL.OZ. | 40 mL

1 TOPICAL ANALGESIC MIST 1 FL.OZ. | 30 mL

1 TOPICAL ANALGESIC BATH SALT SOAK NET WT. 4.2 OZ. | 120 g